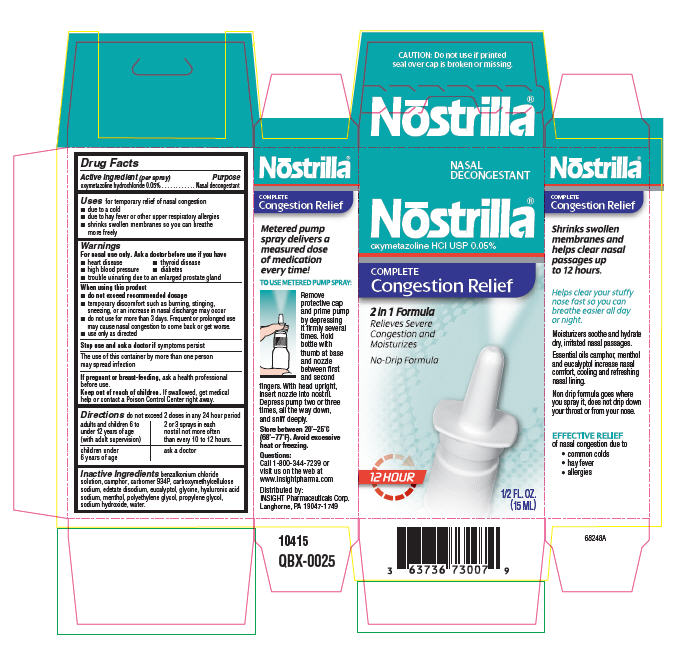 DRUG LABEL: Nostrilla
NDC: 63736-072 | Form: SPRAY, METERED
Manufacturer: Insight Pharmaceuticals
Category: otc | Type: HUMAN OTC DRUG LABEL
Date: 20090619

ACTIVE INGREDIENTS: Oxymetazoline Hydrochloride 0.0005 mL/100 mL
INACTIVE INGREDIENTS: benzalkonium chloride; camphor; carboxymethylcellulose sodium; edetate disodium; eucalyptol; glycine; menthol; polyethylene glycol; propylene glycol; sodium hydroxide; water

Nōstrilla®
oxymetazoline HCl USP 0.05%

Drug Facts

Active Ingredient (per spray)

Purpose

oxymetazoline hydrochloride 0.05% . . . . . . . . . . . . Nasal decongestant

Uses

for temporary relief of nasal congestion

- due to a cold
- due to hay fever or other upper respiratory allergies
- shrinks swollen membranes so you can breathe more freely

Warnings

ASK DOCTOR

For nasal use only. Ask a doctor before use if you have

- heart disease
- thyroid disease
- high blood pressure
- diabetes
- trouble urinating due to an enlarged prostate gland

When using this product

- do not exceed recommended dosage
- temporary discomfort such as burning, stinging, sneezing, or an increase in nasal discharge may occur
- do not use for more than 3 days. Frequent or prolonged use may cause nasal congestion to come back or get worse.
- use only as directed

Stop use and ask a doctor if symptoms persist

The use of this container by more than one person may spread infection

PREGNANCY OR BREAST FEEDING

If pregnant or breast-feeding, ask a health professional before use.

Keep out of reach of children. If swallowed, get medical help or contact a Poison Control Center right away.

Directions

do not exceed 2 doses in any 24 hour period

adults and children 6 to under 12 years of age (with adult supervision) | 2 or 3 sprays in each nostril not more often than every 10 to 12 hours.
children under 6 years of age | ask a doctor

Inactive Ingredients

benzalkonium chloride solution, camphor, carbomer 934P, carboxymethylcellulose sodium, edetate disodium, eucalyptol, glycine, hyaluronic acid sodium, menthol, polyethylene glycol, propylene glycol, sodium hydroxide, water.

PRINCIPAL DISPLAY PANEL - 1/2 FL. OZ. Bottle Carton

NASAL
DECONGESTANT

Nōstrilla®
oxymetazoline HCl USP 0.05%

COMPLETE
Congestion Relief

2 in 1 Formula
Relieves Severe
Congestion and
Moisturizes

No-Drip Formula

12 HOUR

1/2 FL. OZ.
(15 ML)